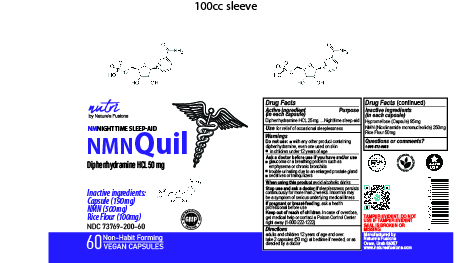 DRUG LABEL: NMNQuil
NDC: 73769-200 | Form: CAPSULE
Manufacturer: NATURE'S FUSIONS, LLC
Category: otc | Type: HUMAN OTC DRUG LABEL
Date: 20230424

ACTIVE INGREDIENTS: DIPHENHYDRAMINE HYDROCHLORIDE 25 mg/1 1
INACTIVE INGREDIENTS: NICOTINAMIDE MONONUCLEOTIDE; HYDROXYPROPYL CELLULOSE, UNSPECIFIED; STARCH, RICE

PURPOSE

for relief of occasional sleeplessness

ACTIVE INGREDIENT

Diphenhydramine HCL 50mg - Nighttime Sleep Aid

Keep out of reach of children. In case of overdose get medical help or contact a Poison Control Center right away.

INDICATIONS AND USAGE

adults and children 12 years of age and over: take 2 capsules (50 mg) at bedtime if needed, or as directed by a doctor

INACTIVE INGREDIENT

Hypromellose (capsule)

NMN (nicotinamide mononucleotide)

Rice Flour

DOSAGE AND ADMINISTRATION

take 2 capsules (50 mg) at bedtime if needed

Do not use with any other product containing diphenhydramine, even one used on skin in children under 12 years of age ■ Ask a doctor before use if you have and/or use glaucoma or a breathing problem such as emphysema or chronic bronchitis trouble urinating due to an enlarged prostate gland sedatives or tranquilizers (in each capsule) ■ When using this product avoid alcoholic drinks Stop use and ask a doctor if sleeplessness persists continuously for more than 2 weeks. Insomnia may be a symptom of serious underlying medical illness If pregnant or breast-feeding, ask a health professional before use Keep out of reach of children. In case of overdose, get medical help or contact a Poison Control Center right away (1-800-222-1222)

PACKAGE LABEL

NMNQuil Inactive ingredients: Capsule (190mg) NMN (500mg) Rice Flour (100mg) Non-Habit Forming 60 VEGAN CAPSULES NMNIGHTTIME SLEEP-AID Drug Facts Active ingredient Purpose Diphenhydramine HCL 25mg. Nighttime sleep-aid Use for relief of occasional sleeplessness Warnings with any other product containing diphenhydramine, even one used on skin in children under 12 years of age Do not use: ■ ■ Ask a doctor before use if you have and/or use glaucoma or a breathing problem such as emphysema or chronic bronchitis trouble urinating due to an enlarged prostate gland sedatives or tranquilizers (in each capsule) ■ When using this product avoid alcoholic drinks Stop use and ask a doctor if sleeplessness persists continuously for more than 2 weeks. Insomnia may be a symptom of serious underlying medical illness If pregnant or breast-feeding, ask a health professional before use Keep out of reach of children. In case of overdose, get medical help or contact a Poison Control Center right away (1-800-222-1222) adults and children 12 years of age and over: take 2 capsules (50 mg) at bedtime if needed, or as directed by a doctor Directions Drug Facts (continued) Inactive ingredients (in each capsule) NMN (Nicotinamide mononucleotide) 250mg Rice Flour 50mg Questions or comments? 1-800-872-9500 TAMPER EVIDENT: DO NOT USE IF TAMPER EVIDENT SEAL IS BROKEN OR MISSING Hypromellose (Capsule) 95mg NDC 73769-200-60 ■■ Manufactured by Nature’s Fusions Orem, Utah 84057 www.naturesfusions.com